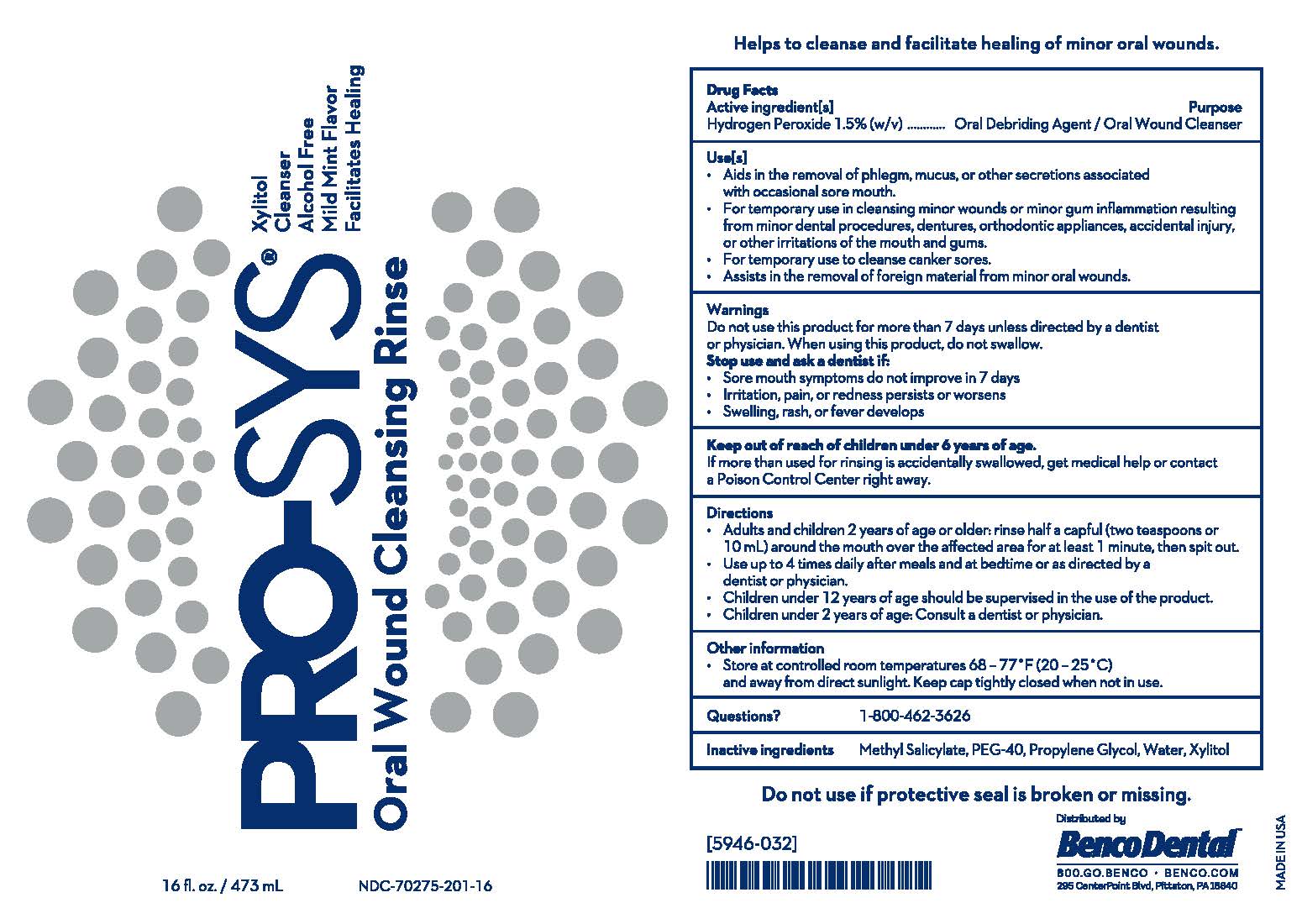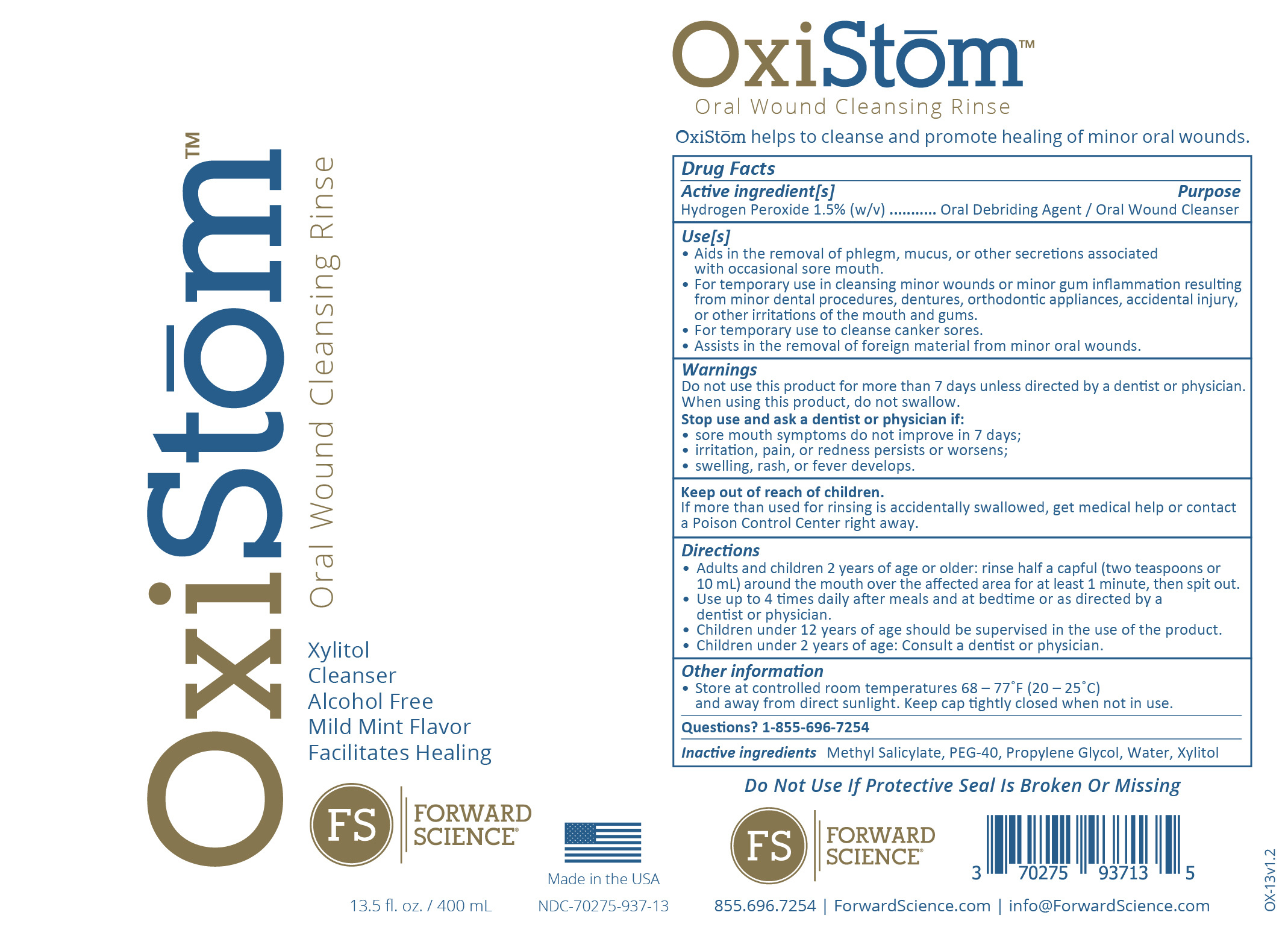 DRUG LABEL: OxiStom
NDC: 70275-937 | Form: LIQUID
Manufacturer: Forward Science Technologies LLC
Category: otc | Type: HUMAN OTC DRUG LABEL
Date: 20251226

ACTIVE INGREDIENTS: HYDROGEN PEROXIDE 15 mg/1 mL
INACTIVE INGREDIENTS: XYLITOL; METHYL SALICYLATE; PROPYLENE GLYCOL; POLYOXYL 40 HYDROGENATED CASTOR OIL; WATER

Inactive Ingredients

Methyl Salicylate, PEG-40, Propylene Glycol, Water, Xylitol

Questions?

1-855-696-7254

Active Ingredient

Hydrogen Peroxide 1.5% (w/v)

Purpose

Oral Debriding Agent / Oral Wound Cleanser

Other Information

Store at controlled room temperatures 68 - 77ºF (20 - 25ºC) and away from direct sunlight. Keep cap tightly closed when not in use.

Uses

• Aids in the removal of phlegm, mucus, or other secretions associated with occasional sore mouth.
• For temporary use in cleansing minor wounds or minor gum inflammation resulting from minor dental procedures, dentures, orthodontic appliances, accidental injury, or other irritations of the mouth and gums.
• For temporary use to cleanse canker sores.
• Assists in the removal of foreign material from minor oral wounds.

Warnings

Do not use this product for more than 7 days unless directed by a dentist or physician. When using this product, do not swallow.
Stop use and ask a dentist or physician if:

• sore mouth symptoms do not improve in 7 days;
• irritation, pain, or redness persists or worsens;
• swelling, rash, or fever develops.

Keep out of reach of children

If more than used for rinsing is accidentally swallowed, get medical help or contact a Poison Control Center right away.

Directions

• Adults and children 2 years of age or older: rinse half a capful (two teaspoons or 10 mL) around the mouth over the affected area for at least 1 minute, then spit out.
• Use up to 4 times daily after meals and at bedtime or as directed by a dentist or physician.
• Children under 12 years of age should be supervised in the use of the product.
• Children under 2 years of age: Consult a dentist or physician.

Directions

• Adults and children 2 years of age or older: rinse half a capful (two teaspoons or 10 mL) around the mouth over the affected area for at least 1 minute, then spit out.
• Use up to 4 times daily after meals and at bedtime or as directed by a dentist or physician.
• Children under 12 years of age should be supervised in the use of the product.
• Children under 2 years of age: Consult a dentist or physician.